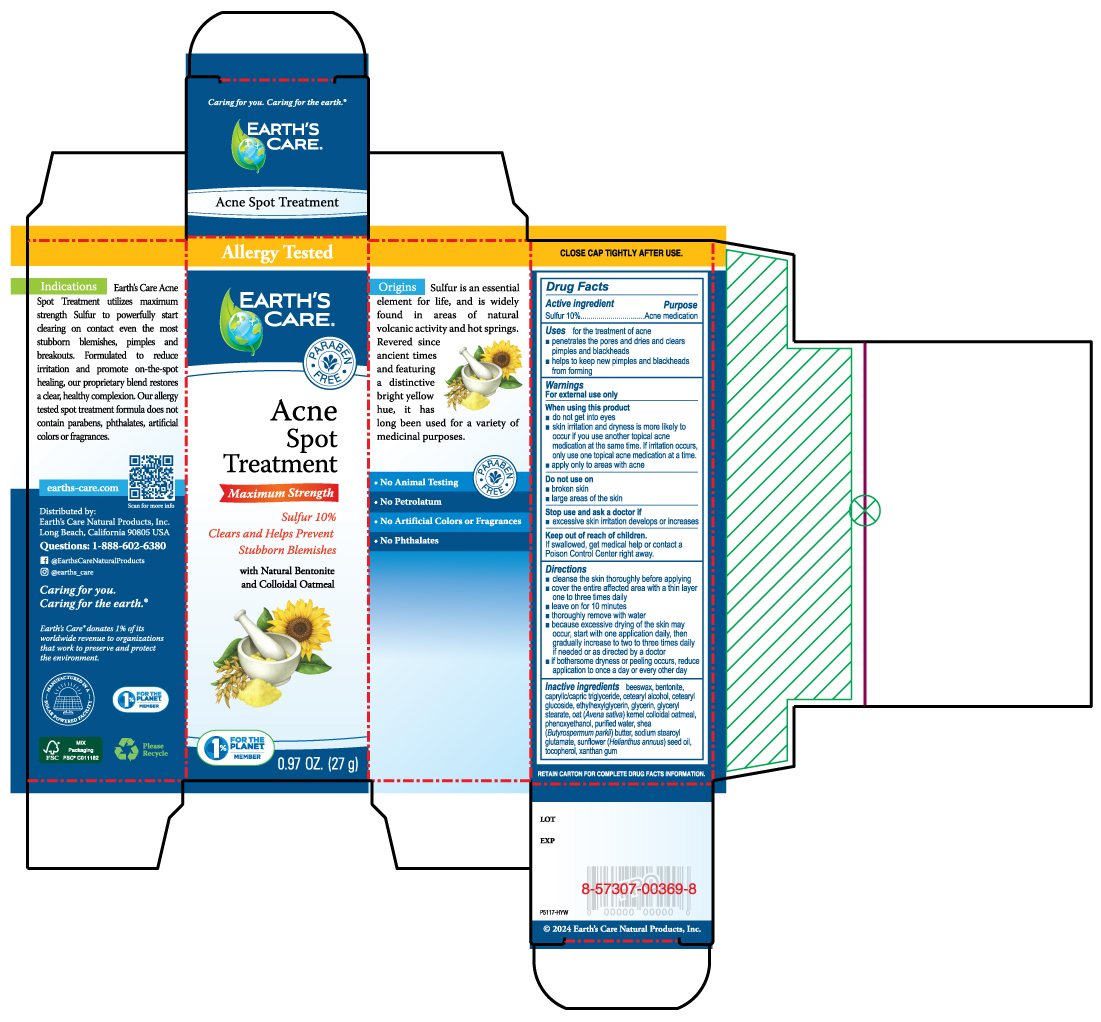 DRUG LABEL: Earths Care Acne Spot Treatment
NDC: 24286-1557 | Form: CREAM
Manufacturer: DLC Laboratories, Inc.
Category: otc | Type: HUMAN OTC DRUG LABEL
Date: 20250515

ACTIVE INGREDIENTS: SULFUR 10 g/100 g
INACTIVE INGREDIENTS: CAPRYLIC/CAPRIC TRIGLYCERIDE; OATMEAL; BENTONITE; SHEA BUTTER; CETEARYL GLUCOSIDE; GLYCERIN; GLYCERYL MONOSTEARATE; SUNFLOWER OIL; PHENOXYETHANOL; WATER; SODIUM STEAROYL GLUTAMATE; XANTHAN GUM; ETHYLHEXYLGLYCERIN; CETEARYL ALCOHOL; BEESWAX; TOCOPHEROL

Earths Care Acne Spot Treatment

Drug Facts

Active ingredient

Sulfur 10%

Purpose

Acne medication

Uses

for the treatment of acne

- penetrates the pores and dries and clears pimples and blackheads
- helps to keep new pimples and blackheads from forming

Warnings

For external use only

When using this product

- do not get into eyes
- skin irritation and dryness is more likely to occur if you use another topical acne medication at the same time. If irritation occurs, only use one topical acne medication at a time.
- apply only to areas with acne

Do not use on

- broken skin
- large areas of the skin

Stop use and ask a doctor if

- excessive skin irritation develops or increases

Keep out of reach of children.

If swallowed, get medical help or contact a Poison Control Center right away.

Directions

- cleanse the skin thoroughly before applying
- cover the entire affected area with a thin layer one to three times daily
- leave on for 10 minutes
- thoroughly remove with water
- because excessive drying of the skin may occur, start with one application daily, then gradually increase to two to three times daily if needed or as directed by a doctor
- if bothersome dryness or peeling occurs, reduce application to once a day or every other day

Inactive ingredients

beeswax, bentonite, caprylic/capric triglyceride, cetearyl alcohol, cetearyl glucoside, ethylhexylglycerin, glycerin, glyceryl stearate, oat (Avena sativa) kernel colloidal oatmeal, phenoxyethanol, purified water, shea (Butyrospermum parkii) butter, sodium stearoyl glutamate, sunflower (Helianthus annuus) seed oil, tocopherol, xanthan gum.

Questions

1-888-602-6380

Distributed by:
Earth's Care Natural Products, Inc.
Long Beach, California 90805 USA

PRINCIPAL DISPLAY PANEL - 27 g Tube Box

Allergy Tested

EARTH'S CARE®

* PARABEN * FREE

Acne Spot Treatment

Maximum Strength

Sulfur 10%

Clears and Helps Prevent
Stubborn Blemishes

with Natural Bentonite
and Colloidal Oatmeal

1% FOR THE PLANET MEMBER

0.97 OZ. (27 g)